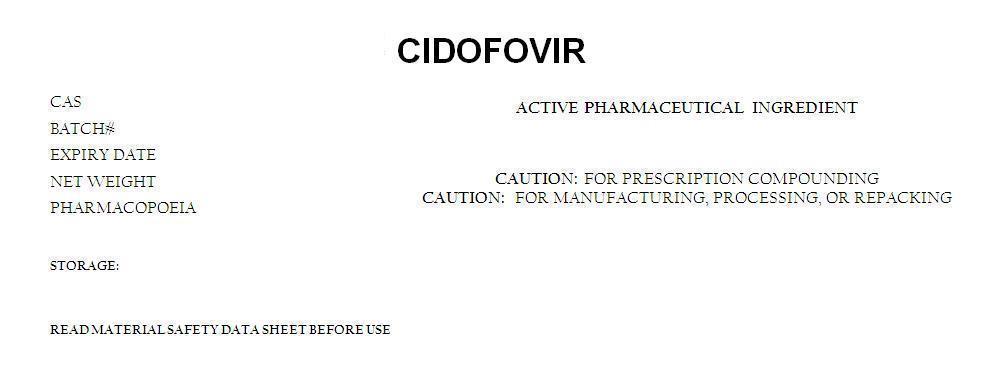 DRUG LABEL: CIDOFOVIR
NDC: 62448-113 | Form: POWDER
Manufacturer: BOSTON SYNTHETICS LIMITED
Category: other | Type: BULK INGREDIENT
Date: 20151201

ACTIVE INGREDIENTS: CIDOFOVIR ANHYDROUS  1 g/1 g

CIDOFOVIR